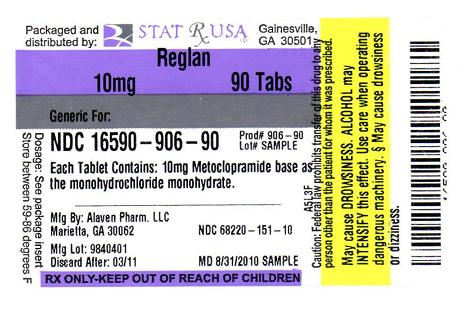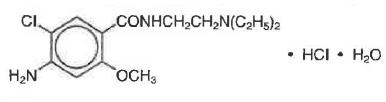 DRUG LABEL: REGLAN
NDC: 16590-906 | Form: TABLET
Manufacturer: STAT RX USA LLC
Category: prescription | Type: HUMAN PRESCRIPTION DRUG LABEL
Date: 20100831

ACTIVE INGREDIENTS: METOCLOPRAMIDE HYDROCHLORIDE 10 mg/1 1
INACTIVE INGREDIENTS: MAGNESIUM STEARATE; CELLULOSE, MICROCRYSTALLINE; MANNITOL; STEARIC ACID

reglan® tablets (metoclopramide tablets, USP)

Rx Only

WARNING: TARDIVE DYSKINESIA

Treatment with metoclopramide can cause tardive dyskinesia, a serious movement disorder that is often irreversible. The risk of developing tardive dyskinesia increases with duration of treatment and total cumulative dose.

Metoclopramide therapy should be discontinued in patients who develop signs or symptoms of tardive dyskinesia. There is no known treatment for tardive dyskinesia. In some patients, symptoms may lessen or resolve after metoclopramide treatment is stopped.

Treatment with metoclopramide for longer than 12 weeks should be avoided in all but rare cases where therapeutic benefit is thought to outweigh the risk of developing tardive dyskinesia.

See WARNINGS

DESCRIPTION

For oral administration, reglan® tablets (metoclopramide tablets, USP) 10 mg are white, scored, capsule-shaped tablets engraved "REGLAN" on one side and "AP 10" on the opposite side.

Each tablet contains:
Metoclopramide base .................................................. 10 mg
(as the monohydrochloride monohydrate)

Inactive Ingredients
Magnesium Stearate, Mannitol, Microcrystalline Cellulose, Stearic Acid.

reglan® tablets (metoclopramide tablets, USP) 5 mg are green, elliptical-shaped tablets engraved "REGLAN" over "5" on one side and "AP" on the opposite side.

Each tablet contains:
Metoclopramide base .................................................... 5 mg
(as the monohydrochloride monohydrate)

Inactive Ingredients
Corn starch, D&C Yellow 10 Aluminum Lake, FD&C Blue 1 Aluminum Lake, Lactose, Microcrystalline Cellulose, Silicon Dioxide, Stearic Acid.

Metoclopramide hydrochloride is a white crystalline, odorless substance, freely soluble in water. Chemically, it is 4-amino-5-chloro-N-[2-(diethylamino)ethyl]-2-methoxy benzamide monohydrochloride monohydrate. Its molecular formula is C14H22ClN3O2•HCl•H2O. Its molecular weight is 354.3.

CLINICAL PHARMACOLOGY

Metoclopramide stimulates motility of the upper gastrointestinal tract without stimulating gastric, biliary, or pancreatic secretions. Its mode of action is unclear. It seems to sensitize tissues to the action of acetylcholine. The effect of metoclopramide on motility is not dependent on intact vagal innervation, but it can be abolished by anticholinergic drugs.

Metoclopramide increases the tone and amplitude of gastric (especially antral) contractions, relaxes the pyloric sphincter and the duodenal bulb, and increases peristalsis of the duodenum and jejunum resulting in accelerated gastric emptying and intestinal transit. It increases the resting tone of the lower esophageal sphincter. It has little, if any, effect on the motility of the colon or gallbladder.

In patients with gastroesophageal reflux and low LESP (lower esophageal sphincter pressure), single oral doses of metoclopramide produce dose-related increases in LESP. Effects begin at about 5 mg and increase through 20 mg (tile largest dose tested). The increase in LESP from a 5 mg dose lasts about 45 minutes and that of 20 mg lasts between 2 and 3 hours. Increased rate of stomach emptying has been observed with single oral doses of 10 mg.

The antiemetic properties of metoclopramide appear to be a result of its antagonism of central and peripheral dopamine receptors. Dopamine produces nausea and vomiting by stimulation of the medullary chemoreceptor trigger zone (CTZ), and metoclopramide blocks stimulation of the CTZ by agents like l-dopa or apomorphine which are known to increase dopamine levels or to possess dopamine-like effects. Metoclopramide also abolishes the slowing of gastric emptying caused by apomorphine.

Like the phenothiazines and related drugs, which are also dopamine antagonists, metoclopramide produces sedation and may produce extrapyramidal reactions, although these are comparatively rare (see WARNINGS). Metoclopramide inhibits the central and peripheral effects of apomorphine, induces release of prolactin and causes a transient increase in circulating aldosterone levels, which may be associated with transient fluid retention.

The onset of pharmacological action of metoclopramide is 1 to 3 minutes following an intravenous dose, 10 to 15 minutes following intramuscular administration, and 30 to 60 minutes following an oral dose; pharmacological effects persist for 1 to 2 hours.

Pharmacokinetics

Metoclopramide is rapidly and well absorbed. Relative to an intravenous dose of 20 mg, the absolute oral bioavailability of metoclopramide is 80% ± 15.5% as demonstrated in a crossover study of 18 subjects. Peak plasma concentrations occur at about 1 to 2 hr after a single oral dose. Similar time to peak is observed after individual doses at steady state.

In a single dose study of 12 subjects, the area under the drug concentration-time curve increases linearly with doses from 20 to 100 mg. Peak concentrations increase linearly with dose; time to peak concentrations remains the same; whole body clearance is unchanged; and the elimination rate remains the same. The average elimination half-life in individuals with normal renal function is 5 to 6 hr. Linear kinetic processes adequately describe the absorption and elimination of metoclopramide.

Approximately 85% of the radioactivity of an orally administered dose appears in the urine within 72 hr. Of the 85% eliminated in the urine, about half is present as free or conjugated metoclopramide.

The drug is not extensively bound to plasma proteins (about 30%). The whole body volume of distribution is high (about 3.5 L/kg) which suggests extensive distribution of drug to the tissues.

Renal impairment affects the clearance of metoclopramide. In a study with patients with varying degrees of renal impairment, a reduction in creatinine clearance was correlated with a reduction in plasma clearance, renal clearance, non-renal clearance, and increase in elimination half-life. The kinetics of metoclopramide in the presence of renal impairment remained linear however. The reduction in clearance as a result of renal impairment suggests that adjustment downward of maintenance dosage should be done to avoid drug accumulation.

Adult Pharmacokinetic Data
Parameter | Value
Vd (Lkg) | - 3.5
Plasma Protein Binding | - 30%
t1/2 (hr) | 5 to 6
Oral Bioavailability | 80% ± 15.5%

In pediatric patients, the pharmacodynamics of metoclopramide following oral and intravenous administration are highly variable and a concentration-effect relationship has not been established.

There are insufficient reliable data to conclude whether the pharmacokinetics of metoclopramide in adults and the pediatric population are similar. Although there are insufficient data to support the efficacy of metoclopramide in pediatric patients with symptomatic gastroesophageal reflux (GER) or cancer chemotherapy-related nausea and vomiting, its pharmacokinetics have been studied in these patient populations.

In an open-label study, six pediatric patients (age range, 3.5 weeks to 5.4 months) with GER received metoclopramide 0.15 mg/kg oral solution every 6 hours for 10 doses. The mean peak plasma concentration of metoclopramide after the tenth dose was 2-fold (56.8 µg/L) higher compared to that observed after the first dose (29 µg/L) indicating drug accumulation with repeated dosing. After the tenth dose, the mean time to reach peak concentrations (2.2 hr), half-life (4.1 hr), clearance (0.67 L/h/kg), and volume of distribution (4.4 L/kg) of metoclopramide were similar to those observed after the first dose. In the youngest patient (age, 3.5 weeks), metoclopramide half-life after the first and the tenth dose (23.1 and 10.3 hr, respectively) was significantly longer compared to other infants due to reduced clearance. This may be attributed to immature hepatic and renal systems at birth.

Single intravenous doses of metoclopramide 0.22 to 0.46 mg/kg (mean, 0.35 mg/kg) were administered over 5 minutes to 9 pediatric cancer patients receiving chemotherapy (mean age, 11.7 years; range, 7 to 14 yr) for prophylaxis of cytotoxic-induced vomiting. The metoclopramide plasma concentrations extrapolated to time zero ranged from 65 to 395 µg/L (mean, 152 µg/L). The mean elimination half-life, clearance, and volume of distribution of metoclopramide were 4.4 hr (range, 1.7 to 8.3 hr), 0.56 L/h/kg (range, 0.12 to 1.20 L/h/kg), and 3.0 L/kg (range, 1.0 to 4.8 L/kg), respectively.

In another study, nine pediatric cancer patients (age range, 1 to 9 yr) received 4 to 5 intravenous infusions (over 30 minutes) of metoclopramide at a dose of 2 mg/kg to control emesis. After the last dose, the peak serum concentrations of metoclopramide ranged from 1060 to 5680 µg/L. The mean elimination half-life, clearance, and volume of distribution of metoclopramide were 4.5 hr (range, 2.0 to 12.5 hr), 0.37 L/h/kg (range, 0.10 to 1.24 L/h/kg), and 1.93 L/kg (range, 0.95 to 5.50 L/kg), respectively.

INDICATIONS AND USAGE

The use of reglan® tablets is recommended for adults only. Therapy should not exceed 12 weeks in duration.

Symptomatic Gastroesophageal Reflux

reglan® tablets are indicated as short-term (4 to 12 weeks) therapy for adults with symptomatic, documented gastroesophageal reflux who fail to respond to conventional therapy.

The principal effect of metoclopramide is on symptoms of postprandial and daytime heartburn with less observed effect on nocturnal symptoms. If symptoms are confined to particular situations, such as following the evening meal, use of metoclopramide as single doses prior to the provocative situation should be considered, rather than using the drug throughout the day. Healing of esophageal ulcers and erosions has been endoscopically demonstrated at the end of a 12-week trial using doses of 15 mg q.i.d. As there is no documented correlation between symptoms and healing of esophageal lesions, patients with documented lesions should be monitored endoscopically.

Diabetic Gastroparesis (Diabetic Gastric Stasis)

reglan® tablets (metoclopramide tablets, USP) is indicated for the relief of symptoms associated with acute and recurrent diabetic gastric stasis. The usual manifestations of delayed gastric emptying (e.g., nausea, vomiting, heartburn, persistent fullness after meals, and anorexia) appear to respond to reglan® within different time intervals. Significant relief of nausea occurs early and continues to improve over a three-week period. Relief of vomiting and anorexia may precede the relief of abdominal fullness by one week or more.

CONTRAINDICATIONS

Metoclopramide should not be used whenever stimulation of gastrointestinal motility might be dangerous, e.g., in the presence of gastrointestinal hemorrhage, mechanical obstruction, or perforation.

Metoclopramide is contraindicated in patients with pheochromocytoma because the drug may cause a hypertensive crisis, probably due to release of catecholamines from the tumor. Such hypertensive crises may be controlled by phentolamine.

Metoclopramide is contraindicated in patients with known sensitivity or intolerance to the drug.

Metoclopramide should not be used in epileptics or patients receiving other drugs which are likely to cause extrapyramidal reactions, since the frequency and severity of seizures or extrapyramidal reactions may be increased.

WARNINGS

Mental depression has occurred in patients with and without prior history of depression. Symptoms have ranged from mild to severe and have included suicidal ideation and suicide. Metoclopramide should be given to patients with a prior history of depression only if the expected benefits outweigh the potential risks.

Extrapyramidal symptoms, manifested primarily as acute dystonic reactions, occur in approximately 1 in 500 patients treated with the usual adult dosages of 30 to 40 mg/day of metoclopramide. These usually are seen during the first 24 to 48 hours of treatment with metoclopramide, occur more frequently in pediatric patients and adult patients less than 30 years of age and are even more frequent at higher doses. These symptoms may include involuntary movements of limbs and facial grimacing, torticollis, oculogyric crisis, rhythmic protrusion of tongue, bulbar type of speech, trismus, or dystonic reactions resembling tetanus. Rarely, dystonic reactions may present as stridor and dyspnea, possibly due to laryngospasm. If these symptoms should occur, inject 50 mg diphenhydramine hydrochloride intramuscularly, and they usually will subside. Benztropine mesylate, 1 to 2 mg intramuscularly, may also be used to reverse these reactions.

Parkinsonian-like symptoms have occurred, more commonly within the first 6 months after beginning treatment with metoclopramide, but occasionally after longer periods. These symptoms generally subside within 2 to 3 months following discontinuance of metoclopramide. Patients with preexisting Parkinson's disease should be given metoclopramide cautiously, if at all, since such patients may experience exacerbation of parkinsonian symptoms when taking metoclopramide.

Tardive Dyskinesia

(see Boxed Warnings)

Treatment with metoclopramide can cause tardive dyskinesia (TD), a potentially irreversible and disfiguring disorder characterized by involuntary movements of the face, tongue, or extremities. Although the risk of TD with metoclopramide has not been extensively studied, one published study reported a TD prevalence of 20% among patients treated for at least 12 weeks. Treatment with metoclopramide for longer than 12 weeks should be avoided in all but rare cases where therapeutic benefit is thought to outweigh the risk of developing TD.

Although the risk of developing TD in the general population may be increased among the elderly, women, and diabetics, it is not possible to predict which patients will develop metoclopramide-induced TD. Both the risk of developing TD and the likelihood that TD will become irreversible increase with duration of treatment and total cumulative dose.

Metoclopramide should be discontinued in patients who develop signs or symptoms of TD. There is no known effective treatment for established cases of TD, although in some patients, TD may remit, partially or completely, within several weeks to months after metoclopramide is withdrawn.

Metoclopramide itself may suppress, or partially suppress, the signs of TD, thereby masking the underlying disease process. The effect of this symptomatic suppression upon the long-term course of TD is unknown. Therefore, metoclopramide should not be used for the symptomatic control of TD.

Neuroleptic Malignant Syndrome (NMS)

There have been rare reports of an uncommon but potentially fatal symptom complex sometimes referred to as Neuroleptic Malignant Syndrome (NMS) associated with metoclopramide. Clinical manifestations of NMS include hyperthermia, muscle rigidity, altered consciousness, and evidence of autonomic instability (irregular pulse or blood pressure, tachycardia, diaphoresis and cardiac arrhythmias).

The diagnostic evaluation of patients with this syndrome is complicated. In arriving at a diagnosis, it is important to identify cases where the clinical presentation includes both serious medical illness (e.g., pneumonia, systemic infection, etc.) and untreated or inadequately treated extrapyramidal signs and symptoms (EPS). Other important considerations in the differential diagnosis include central anticholinergic toxicity, heat stroke, malignant hyperthermia, drug fever and primary central nervous system (CNS) pathology.

The management of NMS should include 1) immediate discontinuation of metoclopramide and other drugs not essential to concurrent therapy, 2) intensive symptomatic treatment and medical monitoring, and 3) treatment of any concomitant serious medical problems for which specific treatments are available. Bromocriptine and dantrolene sodium have been used in treatment of NMS, but their effectiveness have not been established (see ADVERSE REACTIONS).

PRECAUTIONS

General

In one study in hypertensive patients, intravenously administered metoclopramide was shown to release catecholamines; hence, caution should be exercised when metoclopramide is used in patients with hypertension.

Because metoclopramide produces a transient increase in plasma aldosterone, certain patients, especially those with cirrhosis or congestive heart failure, may be at risk of developing fluid retention and volume overload. If these side effects occur at any time during metoclopramide therapy, the drug should be discontinued.

Adverse reactions, especially those involving the nervous system, may occur after stopping the use of reglan®. A small number of patients may experience a withdrawal period after stopping reglan® that could include dizziness, nervousness, and/or headaches.

Information for Patients

The use of reglan® is recommended for adults only. Metoclopramide may impair the mental and/or physical abilities required for the performance of hazardous tasks such as operating machinery or driving a motor vehicle. The ambulatory patient should be cautioned accordingly.

For additional information, patients should be instructed to see the Medication Guide for reglan® tablets.

Drug Interactions

The effects of metoclopramide on gastrointestinal motility are antagonized by anticholinergic drugs and narcotic analgesics. Additive sedative effects can occur when metoclopramide is given with alcohol, sedatives, hypnotics, narcotics, or tranquilizers.

The finding that metoclopramide releases catecholamines in patients with essential hypertension suggests that it should be used cautiously, if at all, in patients receiving monoamine oxidase inhibitors.

Absorption of drugs from the stomach may be diminished (e.g., digoxin) by metoclopramide, whereas the rate and/or extent of absorption of drugs from the small bowel may be increased (e.g., acetaminophen, tetracycline, levodopa, ethanol, cyclosporine).

Gastroparesis (gastric stasis) may be responsible for poor diabetic control in some patients. Exogenously administered insulin may begin to act before food has left the stomach and lead to hypoglycemia. Because the action of metoclopramide will influence the delivery of food to the intestines and thus the rate of absorption, insulin dosage or timing of dosage may require adjustment.

Carcinogenesis, Mutagenesis, Impairment of Fertility

A 77-week study was conducted in rats with oral doses up to about 40 times the maximum recommended human daily dose. Metoclopramide elevates prolactin levels and the elevation persists during chronic administration. Tissue culture experiments indicate that approximately one-third of human breast cancers are prolactin-dependent in vitro, a factor of potential importance if the prescription of metoclopramide is contemplated in a patient with previously detected breast cancer. Although disturbances such as galactorrhea, amenorrhea, gynecomastia, and impotence have been reported with prolactin-elevating drugs, the clinical significance of elevated serum prolactin levels is unknown for most patients. An increase in mammary neoplasms has been found in rodents after chronic administration of prolactin-stimulating neuroleptic drugs and metoclopramide. Neither clinical studies nor epidemiologic studies conducted to date, however, have shown an association between chronic administration of these drugs and mammary tumorigenesis; the available evidence is too limited to be conclusive at this time.

An Ames mutagenicity test performed on metoclopramide was negative.

Pregnancy Category B

TERATOGENIC EFFECTS

Reproduction studies performed in rats, mice and rabbits by the IV., I.M., S.C., and oral routes at maximum levels ranging from 12 to 250 times the human dose have demonstrated no impairment of fertility or significant harm to the fetus due to metoclopramide. There are, however, no adequate and well-controlled studies in pregnant women. Because animal reproduction studies are not always predictive of human response, this drug should be used during pregnancy only if clearly needed.

Nursing Mothers

Metoclopramide is excreted in human milk. Caution should be exercised when metoclopramide is administered to a nursing mother.

Pediatric Use

Safety and effectiveness in pediatric patients have not been established (see OVERDOSAGE).

Care should be exercised in administering metoclopramide to neonates since prolonged clearance may produce excessive serum concentrations (see CLINICAL PHARMACOLOGY - Pharmacokinetics). In addition, neonates have reduced levels of NADH-cytochrome b5 reductase which, in combination with the aforementioned pharmacokinetic factors, make neonates more susceptible to methemoglobinemia (see OVERDOSAGE).

The safety profile of metoclopramide in adults cannot be extrapolated to pediatric patients. Dystonias and other extrapyramidal reactions associated with metoclopramlde are more common in the pediatric population than in adults. (See WARNINGS and ADVERSE REACTIONS - Extrapyramidal Reactions.)

Geriatric Use

Clinical studies of reglan® did not include sufficient numbers of subjects aged 65 and over to determine whether elderly subjects respond differently from younger subjects.

The risk of developing parkinsonian-like side effects increases with ascending dose. Geriatric patients should receive the lowest dose of reglan® that is effective. If parkinsonian-like symptoms develop in a geriatric patient receiving reglan®, reglan® should generally be discontinued before initiating any specific anti-parkinsonian agents (see WARNINGS and DOSAGE AND ADMINISTRATION - For the Relief of Symptomatic Gastroesophageal Reflux).

The elderly may be at greater risk for tardive dyskinesia (see WARNINGS - Tardive Dyskinesia).

Sedation has been reported in reglan® users. Sedation may cause confusion and manifest as oversedation in the elderly (see CLINICAL PHARMACOLOGY, PRECAUTIONS -Information for Patients and ADVERSE REACTIONS - CNS Effects).

reglan® is known to be substantially excreted by the kidney, and the risk of toxic reactions to this drug may be greater in patients with impaired renal function (see DOSAGE AND ADMINISTRATION - Use in Patients with Renal or Hepatic Impairment).

For these reasons, dose selection for an elderly patient should be cautious, usually starting at the low end of the dosing range, reflecting the greater frequency of decreased renal function, concomitant disease, or other drug therapy in the elderly (see DOSAGE AND ADMINISTRATION - For the Relief of Symptomatic Gastroesophageal Reflux and Use in Patients with Renal or Hepatic Impairment).

Other Special Populations

Patients with NADH-cytochrome b5 reductase deficiency are at an increased risk of developing methemoglobinemia and/or sulfhemoglobinemia when metoclopramide is administered. In patients with G6PD deficiency who experience metoclopramide- induced methemoglobinemia, methylene blue treatment is not recommended (see OVERDOSAGE).

ADVERSE REACTIONS

In general, the incidence of adverse reactions correlates with the dose and duration of metoclopramide administration. The following reactions have been reported, although in most instances, data do not permit an estimate of frequency:

CNS Effects

Restlessness, drowsiness, fatigue, and lassitude occur in approximately 10% of patients receiving the most commonly prescribed dosage of 10 mg q.i.d. (see PRECAUTIONS). Insomnia, headache, confusion, dizziness, or mental depression with suicidal ideation (see WARNINGS) occur less frequently. The incidence of drowsiness is greater at higher doses. There are isolated reports of convulsive seizures without clearcut relationship to metoclopramide. Rarely, hallucinations have been reported.

Extrapyramidal Reactions (EPS)

Acute dystonic reactions, the most common type of EPS associated with metoclopramide, occur in approximately 0.2% of patients (1 in 500) treated with 30 to 40 mg of metoclopramide per day. Symptoms include involuntary movements of limbs, facial grimacing, torticollis, oculogyric crisis, rhythmic protrusion of tongue, bulbar type of speech, trismus, opisthotonus (tetanus-like reactions), and, rarely, stridor and dyspnea possibly due to laryngospasm; ordinarily these symptoms are readily reversed by diphenhydramine (see WARNINGS).

Parkinsonian-like symptoms may include bradykinesia, tremor, cogwheel rigidity, mask-like facies (see WARNINGS).

Tardive dyskinesia most frequently is characterized by involuntary movements of the tongue, face, mouth, or jaw, and sometimes by involuntary movements of the trunk and/or extremities; movements may be choreoathetotic in appearance (see WARNINGS).

Motor restlessness (akathisia) may consist of feelings of anxiety, agitation, jitteriness, and insomnia, as well as inability to sit still, pacing, foot tapping. These symptoms may disappear spontaneously or respond to a reduction in dosage.

Neuroleptic Malignant Syndrome

Rare occurrences of neuroleptic malignant syndrome (NMS) have been reported. This potentially fatal syndrome is comprised of the symptom complex of hyperthermia, altered consciousness, muscular rigidity, and autonomic dysfunction (see WARNINGS).

Endocrine Disturbances

Galactorrhea, amenorrhea, gynecomastia, impotence secondary to hyperprolactlnemia (see PRECAUTIONS). Fluid retention secondary to transient elevation of aldosterone (see CLINICAL PHARMACOLOGY).

Cardiovascular

Hypotension, hypertension, supraventricular tachycardia, bradycardia, fluid retention, acute congestive heart failure and possible AV block (see CONTRAINDICATIONS and PRECAUTIONS).

Gastrointestinal

Nausea and bowel disturbances, primarily diarrhea.

Hepatic

Rarely, cases of hepatotoxicity, characterized by such findings as jaundice and altered liver function tests, when metoclopramide was administered with other drugs with known hepatotoxic potential.

Renal

Urinary frequency and incontinence.

Hematologic

A few cases of neutropenia, leukopenia, or agranulocytosis, generally without clearcut relationship to metoclopramide. Methemoglobinemia, in adults and especially with overdosage in neonates (see OVERDOSAGE). Sulfhemoglobinemia in adults.

Allergic Reactions

A few cases of rash, urticaria, or bronchospasm, especially in patients with a history of asthma. Rarely, angioneurotic edema, including glossal or laryngeal edema.

Miscellaneous

Visual disturbances. Porphyria.

OVERDOSAGE

Symptoms of overdosage may include drowsiness, disorientation and extrapyramidal reactions. Anticholinergic or antiparkinson drugs or antihistamines with anticholinergic properties may be helpful in controlling the extrapyramidal reactions. Symptoms are self-limiting and usually disappear within 24 hours.

Hemodialysis removes relatively little metoclopramide, probably because of the small amount of the drug in blood relative to tissues. Similarly, continuous ambulatory peritoneal dialysis does not remove significant amounts of drug. It is unlikely that dosage would need to be adjusted to compensate for losses through dialysis. Dialysis is not likely to be an effective method of drug removal in overdose situations.

Unintentional overdose due to misadministration has been reported in infants and children with the use of metoclopramide oral solution. While there was no consistent pattern to the reports associated with these overdoses, events included seizures, extrapyramidal reactions, and lethargy.

Methemoglobinemia has occurred in premature and full-term neonates who were given overdoses of metoclopramide (1 to 4 mg/kg/day orally, intramuscularly or intravenously for 1 to 3 or more days). Methemoglobinemia can be reversed by the intravenous administration of methylene blue. However, methylene blue may cause hemolytic anemia in patients with G6PD deficiency, which may be fatal (see PRECAUTIONS-Other Special Populations).

DOSAGE AND ADMINISTRATION

Therapy with reglan® tablets should not exceed 12 weeks in duration.

For the Relief of Symptomatic Gastroesophageal Reflux

Administer from 10 mg to 15 mg reglan® (metoclopramide hydrochloride, USP) orally up to q.i.d. 30 minutes before each meal and at bedtime, depending upon symptoms being treated and clinical response (see CLINICAL PHARMACOLOGY and INDICATIONS AND USAGE). If symptoms occur only intermittently or at specific times of the day, use of metoclopramide in single doses up to 20 mg prior to the provoking situation may be preferred rather than continuous treatment. Occasionally, patients (such as elderly patients) who are more sensitive to the therapeutic or adverse effects of metoclopramide will require only 5 mg per dose.

Experience with esophageal erosions and ulcerations is limited, but healing has thus far been documented in one controlled trial using q.i.d. therapy at 15 mg/dose, and this regimen should be used when lesions are present, so long as it is tolerated (see ADVERSE REACTIONS). Because of the poor correlation between symptoms and endoscopic appearance of the esophagus, therapy directed at esophageal lesions is best guided by endoscopic evaluation.

Therapy longer than 12 weeks has not been evaluated and cannot be recommended.

For the Relief of Symptoms Associated with Diabetic Gastroparesis (Diabetic Gastric Stasis)

Administer 10 mg of metoclopramide 30 minutes before each meal and at bedtime for two to eight weeks, depending upon response and the likelihood of continued well-being upon drug discontinuation.

The initial route of administration should be determined by the severity of the presenting symptoms. If only the earliest manifestations of diabetic gastric stasis are present, oral administration of reglan® may be initiated. However, if severe symptoms are present, therapy should begin with metoclopramide injection (consult labeling of the injection prior to initiating parenteral administration).

Administration of metoclopramide injection up to 10 days may be required before symptoms subside, at which time oral administration may be instituted. Since diabetic gastric stasis is frequently recurrent, reglan® therapy should be reinstituted at the earliest manifestation.

Use in Patients with Renal or Hepatic Impairment

Since metoclopramide is excreted principally through the kidneys, in those patients whose creatinine clearance is below 40 mL/min, therapy should be initiated at approximately one-half the recommended dosage. Depending upon clinical efficacy and safety considerations, the dosage may be increased or decreased as appropriate.

See OVERDOSAGE section for information regarding dialysis.

Metoclopramide undergoes minimal hepatic metabolism, except for simple conjugation. Its safe use has been described in patients with advanced liver disease whose renal function was normal.

HOW SUPPLIED

Each white, capsule-shaped, scored reglan® tablet (metoclopramide tablets, USP) contains 10 mg metoclopramide base (as the monohydrochloride monohydrate). Available in:

Bottles of 100 tablets (NDC 68220-151-10)

Each green, elliptical-shaped reglan® tablet (metoclopramide tablets, USP) contains 5 mg metoclopramide base (as the monohydrochloride monohydrate). Available in:

Bottles of 100 tablets (NDC 68220-150-10)

STORAGE AND HANDLING

Dispense tablets in tight, light-resistant container.

Tablets should be stored at controlled room temperature, between 20°C and 25°C (68°F and 77°F).

Manufactured for:
ALAVEN®
PHARMACEUTICAL LLC
Marietta, GA 30062

For Medical Inquiries, call toll-free 1-888-317-0001

www.alavenpharm.com

Rev. 07/2009
PCS 9360
6-151-10-16-1009

Medication Guide

REGLAN (REG-lan) Tablets
(metoclopramide tablets)

Read the Medication Guide that comes with REGLAN before you start taking it and each time you get a refill. There may be new information. If you take another product that contains metoclopramide (such as REGLAN injection, REGLAN ODT, or metoclopramide oral syrup), you should read the Medication Guide that comes with that product. Some of the information may be different. This Medication Guide does not take the place of talking with your doctor about your medical condition or your treatment.

What is the most important information I should know about REGLAN?

REGLAN can cause serious side effects, including:

Abnormal muscle movements called tardive dyskinesia (TD). These movements happen mostly in the face muscles. You can not control these movements. They may not go away even after stopping REGLAN. There is no treatment for TD, but symptoms may lessen or go away over time after you stop taking REGLAN.

Your chances for getting TD go up:

- the longer you take REGLAN and the more REGLAN you take. You should not take REGLAN for more than 12 weeks.
- if you are older, especially if you are a woman
- if you have diabetes

It is not possible for your doctor to know if you will get TD if you take REGLAN.

Call your doctor right away if you get movements you can not stop or control, such as:

- lip smacking, chewing, or puckering up your mouth
- frowning or scowling
- sticking out your tongue
- blinking and moving your eyes
- shaking of your arms and legs

See the section "What are the possible side effects of REGLAN?" for more information about side effects.

What is REGLAN?

REGLAN is a prescription medicine used:

- in adults for 4 to 12 weeks to relieve heartburn symptoms with gastroesophageal reflux disease (GERD) when certain other treatments do not work. REGLAN relieves daytime heartburn and heartburn after meals. It also helps ulcers in the esophagus to heal.
- to relieve symptoms of slow stomach emptying in people with diabetes. REGLAN helps treat symptoms such as nausea, vomiting, heartburn, feeling full long after a meal, and loss of appetite. Not all these symptoms get better at the same time.

It is not known if REGLAN is safe and works in children.

Who should not take REGLAN?

Do not take REGLAN if you:

- have stomach or intestine problems that could get worse with REGLAN, such as bleeding, blockage or a tear in the stomach or bowel wall
- have an adrenal gland tumor called a pheochromocytoma
- are allergic to REGLAN or anything in it. See the end of this Medication Guide for a list of ingredients in REGLAN.
- take medicines that can cause uncontrolled movements, such as medicines for mental illness
- have seizures

What should I tell my doctor before taking REGLAN?

Tell your doctor about all your medical conditions, including if you have:

- depression
- Parkinson's disease
- high blood pressure
- kidney problems. Your doctor may start with a lower dose.
- liver problems or heart failure. REGLAN may cause your body to hold fluids.
- diabetes. Your dose of insulin may need to be changed.
- breast cancer
- you are pregnant or plan to become pregnant. It is not known if REGLAN will harm your unborn baby.
- you are breast-feeding. REGLAN can pass into breast milk and may harm your baby. Talk with your doctor about the best way to feed your baby if you take REGLAN.

Tell your doctor about all the medicines you take, including prescription and non-prescription medicines, vitamins, and herbal supplements. REGLAN and some other medicines may interact with each other and may not work as well, or cause possible side effects. Do not start any new medicines while taking REGLAN until you talk with your doctor.

Especially tell your doctor if you take:

- another medicine that contains metoclopramide, such as REGLAN ODT, or metoclopramide oral syrup
- a blood pressure medicine
- a medicine for depression, especially an Monoamine Oxidase Inhibitor (MAOI)
- insulin
- a medicine that can make you sleepy, such as anti-anxiety medicine, sleep medicines, and narcotics.

If you are not sure if your medicine is one listed above, ask your doctor or pharmacist.

Know the medicines you take. Keep a list of them and show it to your doctor and pharmacist when you get a new medicine.

How should I take REGLAN?

- REGLAN comes as a tablet you take by mouth.
- Take REGLAN exactly as your doctor tells you. Do not change your dose unless your doctor tells you.
- You should not take REGLAN for more than 12 weeks.
- If you take too much REGLAN, call your doctor or Poison Control Center right away.

What should I avoid while taking REGLAN?

- Do not drink alcohol while taking REGLAN. Alcohol may make some side effects of REGLAN worse, such as feeling sleepy.
- Do not drive, work with machines, or do dangerous tasks until you know how REGLAN affects you. REGLAN may cause sleepiness.

What are the possible side effects of REGLAN?

Reglan can cause serious side effects, including:

- Abnormal muscle movements. See "What is the most important information I need to know about REGLAN?"
- Uncontrolled spasms of your face and neck muscles, or muscles of your body, arms, and legs (dystonia). These muscle spasms can cause abnormal movements and body positions. These spasms usually start within the first 2 days of treatment. These spasms happen more often in children and adults under age 30.
- Depression, thoughts about suicide, and suicide. Some people who take REGLAN become depressed. You may have thoughts about hurting or killing yourself. Some people who take Reglan have ended their own lives (suicide).
- Neuroleptic Malignant Syndrome (NMS). NMS is a very rare but very serious condition that can happen with Reglan. NMS can cause death and must be treated in a hospital. Symptoms of NMS include: high fever, stiff muscles, problems thinking, very fast or uneven heartbeat, and increased sweating.
- Parkinsonism. Symptoms include slight shaking, body stiffness, trouble moving or keeping your balance. If you already have Parkinson's disease, your symptoms may become worse while you are receiving REGLAN.

Call your doctor and get medical help right away if you:

- feel depressed or have thoughts about hurting or killing yourself
- have high fever, stiff muscles, problems thinking, very fast or uneven heartbeat, and increased sweating
- have muscle movements you cannot stop or control
- have muscle movements that are new or unusual

Common side effects of Reglan include:

- feeling restless, sleepy, tired, dizzy, or exhausted
- headache
- confusion
- trouble sleeping

You may have more side effects the longer you take REGLAN and the more REGLAN you take. You may still have side effects after stopping REGLAN. You may have symptoms from stopping (withdrawal) REGLAN such as headaches, and feeling dizzy or nervous.

Tell your doctor about any side effects that bother you or do not go away. These are not all the possible side effects of REGLAN.

Call your doctor for medical advice about side effects. You may report side effects to FDA at 1-800-FDA-1088.

How should I store REGLAN?

- Keep REGLAN at room temperature between 68°F to 77°F (20°C to 25°C).
- Keep REGLAN in the bottle it comes in. Keep the bottle closed tightly.

Keep REGLAN and all medicines out of the reach of children.

General information about REGLAN

Medicines are sometimes prescribed for purposes other than those listed in a Medication Guide. Do not use REGLAN for a condition for which it was not prescribed. Do not give REGLAN to other people, even if they have the same symptoms that you have. It may harm them.

This Medication Guide summarizes the most important information about REGLAN. If you would like more information, talk with your doctor. You can ask your doctor or pharmacist for information about REGLAN that is written for health professionals. For more information, go to www.alavenpharm.com or call 1-888-317-0001.

What are the ingredients in REGLAN?

Active ingredient: metoclopramide

Inactive ingredients:

REGLAN 10 mg tablets: magnesium stearate, mannitol, microcrystalline cellulose, stearic acid
REGLAN 5 mg tablets: corn starch, D&C yellow 10 aluminum lake, FD&C blue 1 aluminum lake, lactose, microcrystalline cellulose, silicon dioxide, stearic acid

Manufactured for:
ALAVEN®
PHARMACEUTICAL LLC
Marietta, GA 30062

For Medical Inquiries, call toll-free 1-888-317-0001
www.alavenpharm.com

Rev. 07/2009
PCS 9360
6-151-10-16-1009

Revised July 2009

This Medication Guide has been approved by the U.S. Food and Drug Administration.

PACKAGE LABEL

REGLAN 10MG LABEL IMAGE